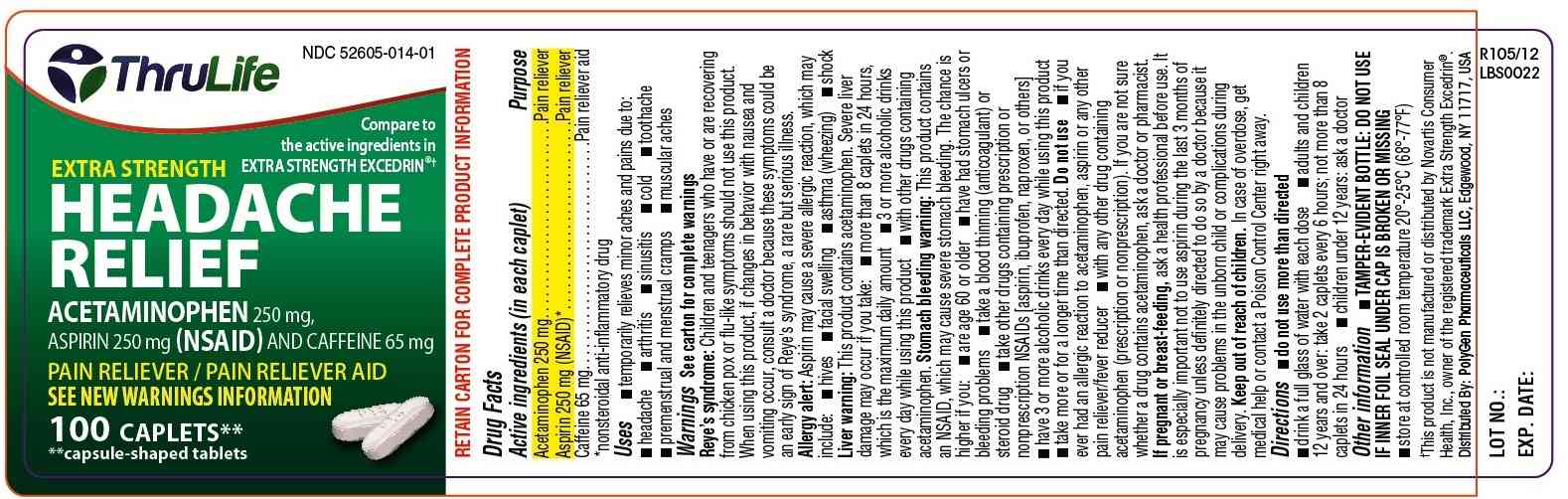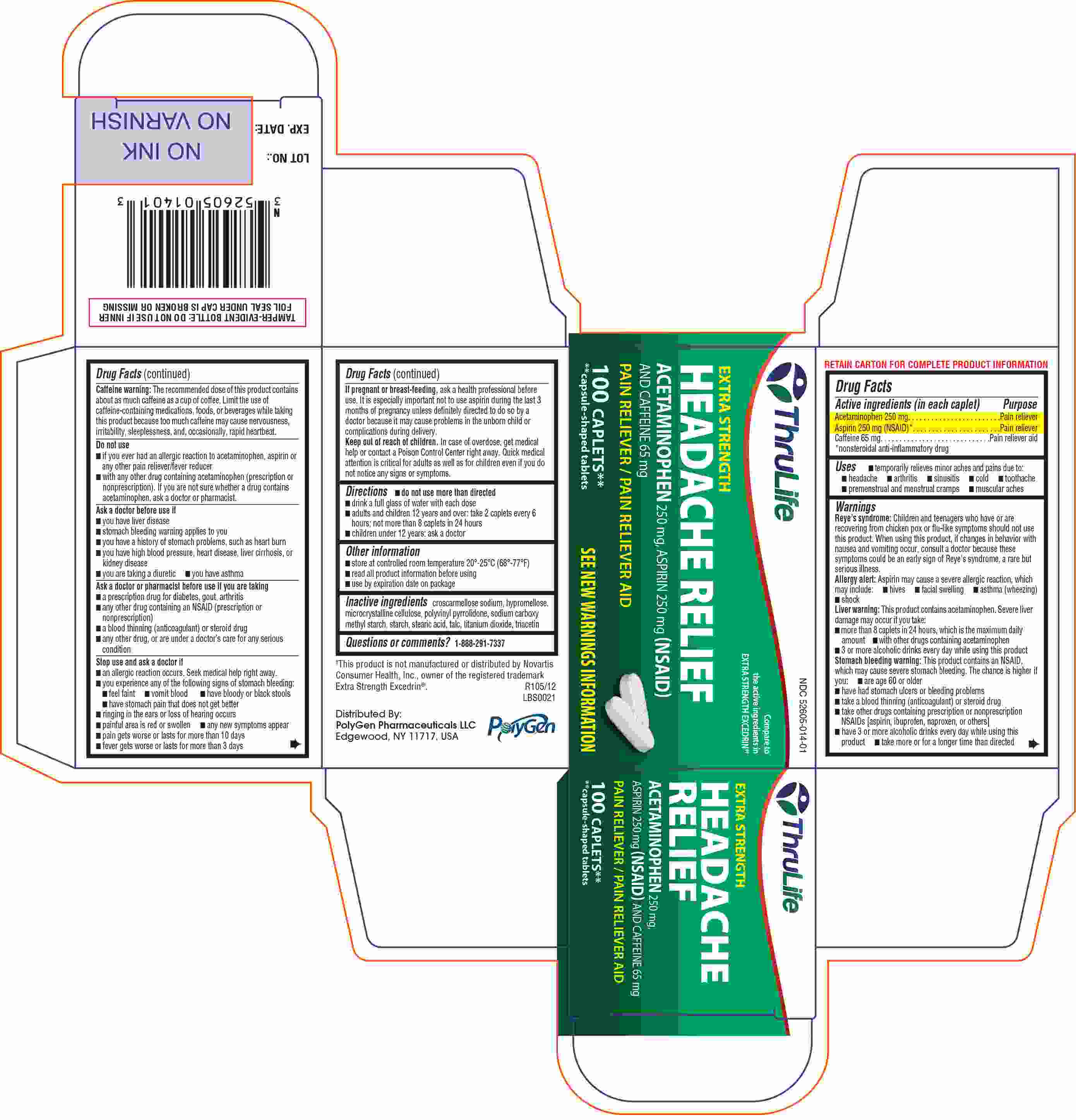 DRUG LABEL: THRULIFE EXTRA STRENGTH HEADACHE RELIEF
NDC: 52605-014 | Form: TABLET
Manufacturer: Polygen Pharmaceuticals LLC
Category: otc | Type: Human OTC Drug Label
Date: 20121212

ACTIVE INGREDIENTS: ACETAMINOPHEN 250 mg/1 1; CAFFEINE 65 mg/1 1; ASPIRIN 250 mg/1 1
INACTIVE INGREDIENTS: CELLULOSE, MICROCRYSTALLINE; CROSCARMELLOSE SODIUM; STEARIC ACID; HYPROMELLOSES; TITANIUM DIOXIDE; TRIACETIN; TALC

THRULIFE EXTRA STRENGTH HEADACHE RELIEF

Active ingredient(s)

(in each caplet)
Acetaminophen 250 mg
Aspirin 250 mg (NSAID)*
Caffeine 65 mg
*nonsteroidal anti-inflammatory drug

Purpose

Pain reliever
Pain reliever
Pain reliever aid

Use(s)

temporarily relieves minor headaches and pains due to: ●headache ● muscular aches ● premenstrual & menstrual cramps ● cold● sinusitis ● arthritis ● toothache

Warnings

Reye's Syndrome: Children and teenagers who have or are recovering from chicken pox or flu like symptoms should not use this product. When using this product, if changes in behavior with nausea and vomiting occur, consult a doctor because these symptoms could be an early sign of Reye’s syndrome, a rare but serious illness.

Allergy alert: Aspirin may cause a severe allergic reaction which may include:

- hives · facial swelling ·asthma (wheezing) · shock

Liver Warning: This product contains acetaminophen.

Severe liver damage may occur if you take · more than 8 tablets in 24 hours, which is the maximum daily amount · with other drugs containing acetaminophen · 3 or more alcoholic drinks every day while using this product.

Stomach bleeding warning: This product contains an NSAID, which may cause severe stomach bleeding. The chance is higher if you ·are age 60 or older ·have had stomach ulcers or bleeding problems · take a blood thinning (anticoagulant) or steroid drug ·take other drugs containing prescription or nonprescription NSAIDs (aspirin, ibuprofen, naproxen, or others) ·have 3 or more alcoholic drinks every day while using this product ·take more or for a longer time than directed.

Caffeine warning: The recommended dose of this product contains about as much caffeine as a cup of coffee. Limit the use of caffeine-containing medications, foods, or beverages while taking this product because too much caffeine may cause nervousness, irritability, sleeplessness, and occasionally, rapid heartbeat.

Do not use

- if you have ever had an allergic reaction to acetaminophen, aspirin or any other pain reliever/fever reducer ·with any other drug containing acetaminophen (prescription or nonprescription).If you are not sure whether a drug contains acetaminophen, ask a doctor or pharmacist.

Ask a doctor before use if

·you have liver disease ·stomach bleeding warning applies to you ·you have a history of stomach problems, such as heart burn ·you have high blood pressure, heart disease, liver cirrhosis, or kidney disease ·you are taking a diuretic ·you have asthma

Ask a doctor or pharmacist before use if

- a prescription drug fordiabetes, gout, arthritis
- any other drug containing an NSAID (prescription or nonprescription) · a blood thinning (anticoagulant) or steroid drug ·any other drug, or are under a doctor’s care for any serious condition.

Stop use and ask doctor if

- an allergic reaction occurs. Seek medical help right away.
- you experience any of the following signs of stomach bleeding:

· feel faint · vomit blood · have bloody or black stools ·have stomach pain that does not get better.

- painful area is red or swollen
- any few symptoms appear ·ringing in the ears or loss of hearing occurs.

●pain gets worse or lasts for more than 10 days ● fever gets worse or lasts for more than 3 days

Pregnancy/Breastfeeding

ask a health professional before use. It is especially important not to use aspirin during the last 3 months of pregnancy unless definitely directed to do so by a

doctor because it may cause problems in the unborn child or complications during delivery.

Keep out of reach of children

In case of overdose, get medical help or contact a poison control center right away. Quick medical attention is critical for adults as well as for children even if you do not notice any signs or symptoms.

Directions

- do not use more than directed ·drink a full glass of water with each dose ·adults and children 12 years and over: take 2 caplets every 6 hours: not more than 8 caplets in 24 hours ·
- children under 12 years of age: ask a doctor.

Other information

- store at controlled room temperature 20º-25ºC (68º-77ºF)
- read all product information before using.
- use by expiration date on package

Inactive ingredients

Microcrystalline cellulose, Croscarmellose sodium, Stearic acid, Hypromellose, Traicetin, Titanium dioxide & Talc

Dosage & Administration section

- Adults and children 12 years and over: Take 2 caplets every 6 hours; not more than 8 caplets in 24 hours.
- Children under 12 years: ask a doctor

OTC - Questions section

1-888-291-7337

Principal Display Panel

Bottle label PDP
EXTRA STRENGTH HEADACHE RELIEF
Carton label PDP
EXTRA STRENGTH HEADACHE RELIEF